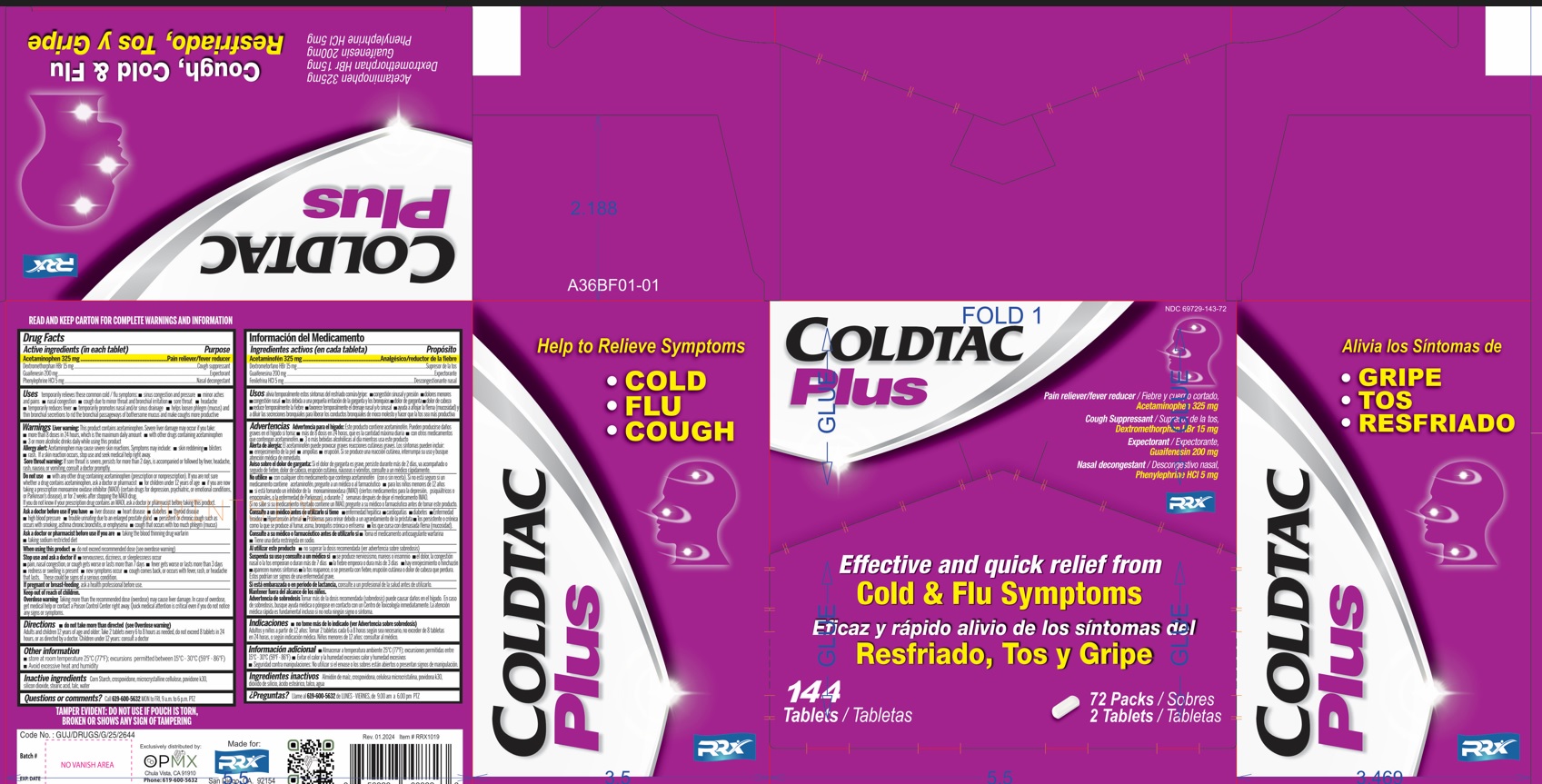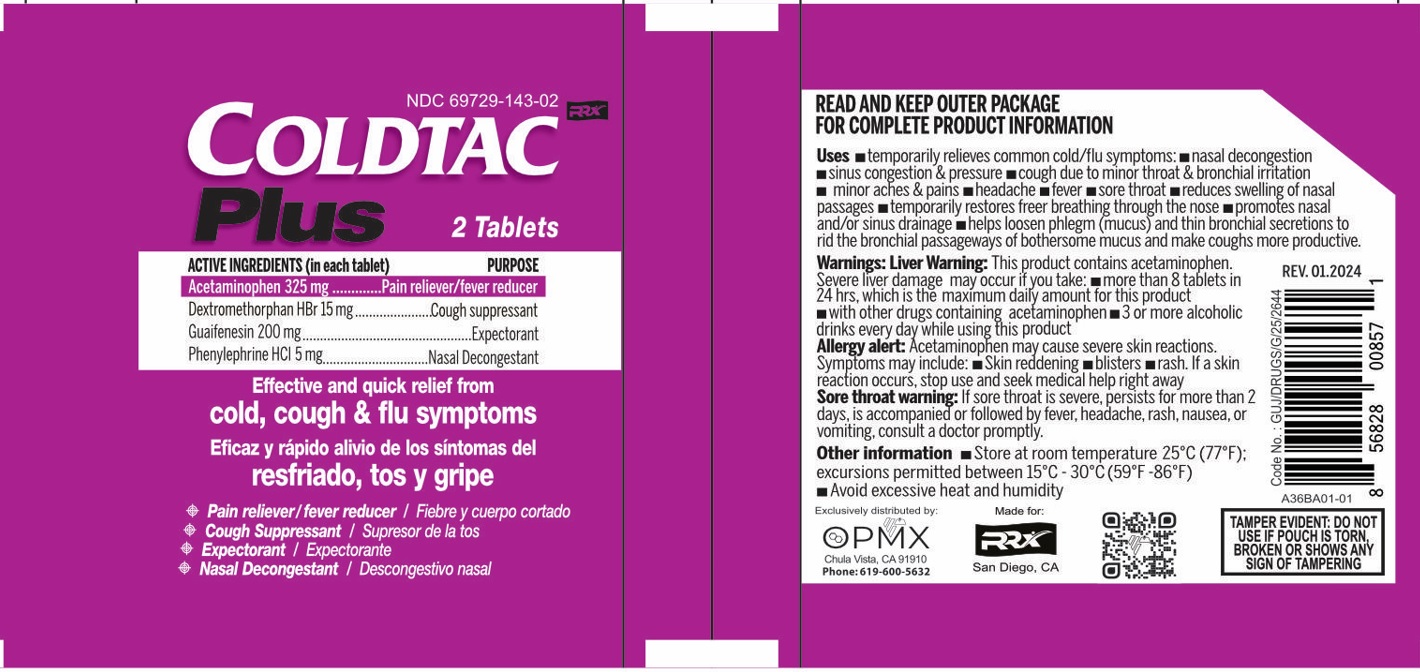 DRUG LABEL: COLDTAC Plus
NDC: 69729-143 | Form: TABLET
Manufacturer: OPMX LLC
Category: otc | Type: HUMAN OTC DRUG LABEL
Date: 20240220

ACTIVE INGREDIENTS: ACETAMINOPHEN 325 mg/1 1; PHENYLEPHRINE HYDROCHLORIDE 5 mg/1 1; DEXTROMETHORPHAN HYDROBROMIDE 15 mg/1 1; GUAIFENESIN 200 mg/1 1
INACTIVE INGREDIENTS: SILICON DIOXIDE; POVIDONE K30; MICROCRYSTALLINE CELLULOSE; STARCH, CORN; STEARIC ACID; CROSPOVIDONE; TALC; WATER

COLDTAC Plus

Active Ingredients (in each tablet)

Acetaminophen USP 325mg.........................................................Pain reliever/fever reducer

Guaifenesin USP 200mg..............................................................Expectorant

Phenylephrine HCL USP 5mg........................................................Decongestant

Dextromethorphan HBr USP 15mg................................................Antitussive

Purpose

Pain reliever/ fever reducer

Expectorant

Decongestant

Antitussive

Uses

Temporarily

- Relieves nasal congestion due to the common cold, hay fever or other upper respiratory allergies
- Relieves sinus congestion and pressure, helps decongest sinus openings and passages
- Restores freer breathing
- Helps loosen bothersome mucus, drain bronchial tubes, and make coughs more productive
- Suppresses cough due to minor throat and bronchial irritation associated with a cold or inhaled irritants
- Temporarily relieves minor aches, pains and fever associated with: headache, common cold, toothache, backache, muscular aches, menstrual cramps

Warnings:

Liver Warning:

This product contains acetaminophen. Severe liver damage may occur if you take:

- More than 8 tablets in 24 hours
- With other drugs containing acetaminophen (prescription or nonprescription). Ask a doctor or pharmacist before using with other drugs if you are not sure
- 3 or more alcoholic drinks every day while using this product

Allergy alert: Acetaminophen may cause severe skin reactions. Symptoms may include:

- skin reddening
- blisters
- rash

If a skin reactio occurs, stop use and seek medical help right away

Sore throat warning: If sore throat is severe, persists for more than 2 days, is accompanied or followed by fever, headache, rash, nausea, or vomiting, consult a doctor promptly

Do not use

- with any other product containing acetaminophen (prescription or nonprescription).

If you are not sure whether a drug contains acetaminophen, ask a doctor or pharmacist.

- if you are now taking a presription monoamine oxidase inhibitor (MAOI) (certain drugs for depression, psychiatric or emotional conditions, or Parkinson's disease), or for 2 weeks after stopping MAOI drug. If you do not know if your prescription drug contains an MAOI, ask a doctor or pharmacist before taking this product.
- for more than 7 days for pain and 3 days for fever, unless directed by a doctor

Ask a doctor before use

if you have

- liver disease
- heart disease
- high blood pressure
- thyroid disease
- diabetes
- trouble urinating due to enlarged prostate gland
- a cough that is accompanied by excessive phlegm (mucus)
- a persistent or chronic cough such as occurs with smoking, asthma or emphysema

Ask a doctor or pharmacist

before use if you are

- taking the blood thinning drug warfarin

Stop use and ask a doctor if

- new symptoms occur
- redness or swelling is present
- pain or fever persists or gets worse
- nervousness, dizziness, or sleeplessness occur
- a persistent cough or symptoms do not improve within 7 days, tends to recur, or is accompanied by fever, rash, or persistent headache. These could be signs of a serious condition.

If pregnant or breast-feeding,

ask a health professional before use.

KEEP OUT OF REACH OF CHILDREN

In case of accidental overdose, get medical help or contact a Poison Control Center right away. Prompt medical attention is critical for adults as well as for children even if you do not notice any signs or symptoms

Directions:

- do not exceed recommended dosage
- adults and children 12 years of age and over:

take 2 tablets every 6 - 8 hours; do not exceed 8 tablets in a 24-hour period

- children under 12 years of age: consult a doctor

Other Information

- store at room temperature 59° to 86°F (15° to 30°C)
- Avoid excessive heat and humidity

TAMPER EVIDENCE: Do not use if packet is open or torn.

Inactive Ingredients

Corn starch, crospovidone, microcrystalline cellulose, povidone k30, silicon dioxide, stearic acid, talc, water

Questions & comments?

Call: 619-600-5632 (Mon-Fri 9am - 5pm EST)

NDC 69729-143-06

COLDTAC Plus

Tablets

Acetaminophen 325 mg / Guaifenesin 200 mg

Dextromethorphan HBr 15 mg / Phenylephrine HCl 5 mg

Effective and quick relief from

cough, cold & flu symptoms

Pain reliever, fever reducer

Nasal Decongestant

Cough Suppressant

Expectorant

Contents 12 Tablets

Exclusively distributed by OPMX

San Diego, CA 92154

Phone: 619-600-5632